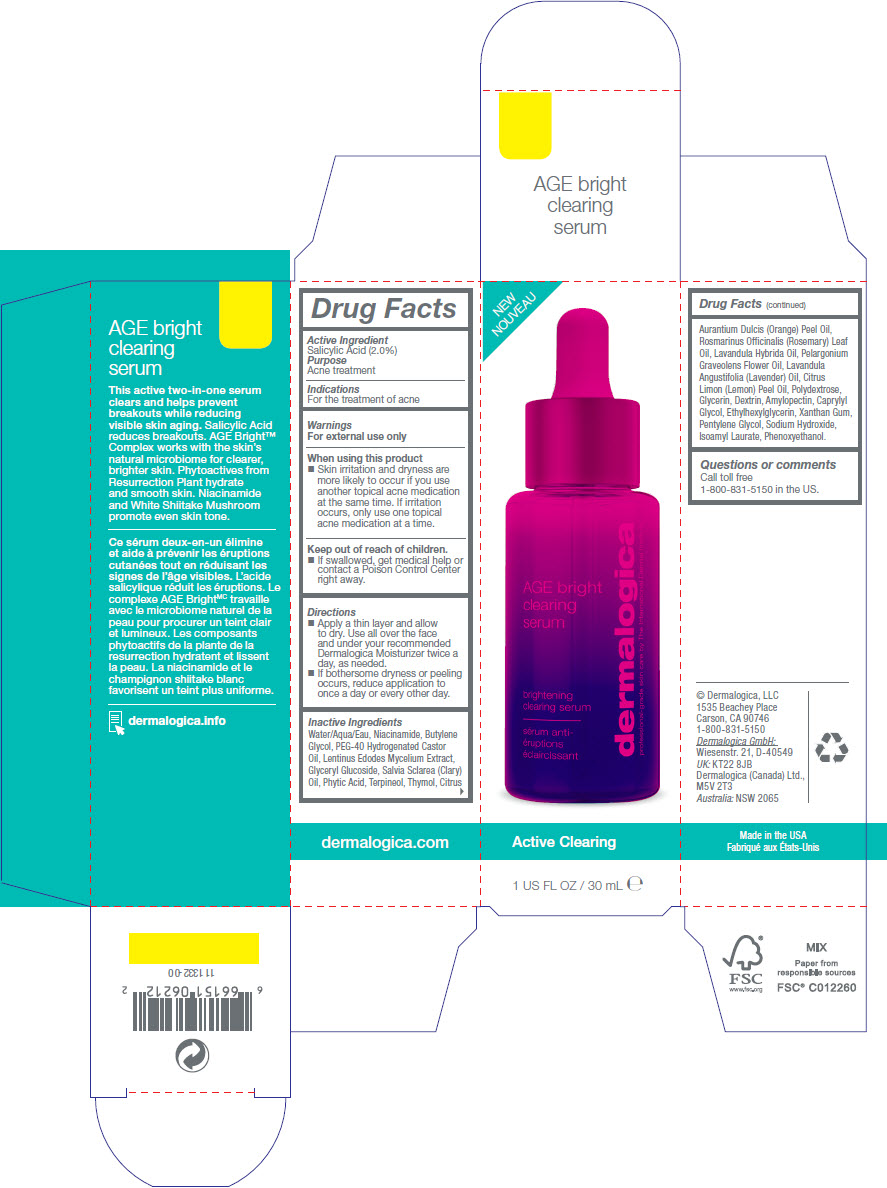 DRUG LABEL: AGE Bright Clearing Serum
NDC: 68479-184 | Form: LIQUID
Manufacturer: Dermalogica, Inc
Category: otc | Type: HUMAN OTC DRUG LABEL
Date: 20241224

ACTIVE INGREDIENTS: Salicylic Acid 20 mg/1 mL
INACTIVE INGREDIENTS: Water; Niacinamide; BUTYLENE GLYCOL; POLYOXYL 40 HYDROGENATED CASTOR OIL; LENTINULA EDODES MYCELIUM; CLARY SAGE OIL; FYTIC ACID; Terpineol; Thymol; ORANGE OIL, COLD PRESSED; ROSEMARY OIL; LAVANDIN OIL; Pelargonium Graveolens Flower Oil; LAVENDER OIL; LEMON OIL, COLD PRESSED; Polydextrose; Glycerin; DEXTRIN PALMITATE (CORN; 20000 MW); AMYLOPECTIN, UNSPECIFIED SOURCE; Caprylyl Glycol; Ethylhexylglycerin; Xanthan Gum; Pentylene Glycol; Sodium Hydroxide; Isoamyl Laurate; Phenoxyethanol

AGE Bright Clearing Serum

Drug Facts

Active Ingredient

Salicylic Acid (2.0%)

Purpose

Acne treatment

Indications

For the treatment of acne

Warnings

For external use only

When using this product

- Skin irritation and dryness are more likely to occur if you use another topical acne medication at the same time. If irritation occurs, only use one topical acne medication at a time.

Keep out of reach of children.

- If swallowed, get medical help or contact a Poison Control Center right away.

Directions

- Apply a thin layer and allow to dry. Use all over the face and under your recommended Dermalogica Moisturizer twice a day, as needed.
- If bothersome dryness or peeling occurs, reduce application to once a day or every other day.

Inactive Ingredients

Water/Aqua/Eau, Niacinamide, Butylene Glycol, PEG-40 Hydrogenated Castor Oil, Lentinus Edodes Mycelium Extract, Glyceryl Glucoside, Salvia Sclarea (Clary) Oil, Phytic Acid, Terpineol, Thymol, Citrus Aurantium Dulcis (Orange) Peel Oil, Rosmarinus Officinalis (Rosemary) Leaf Oil, Lavandula Hybrida Oil, Pelargonium Graveolens Flower Oil, Lavandula Angustifolia (Lavender) Oil, Citrus Limon (Lemon) Peel Oil, Polydextrose, Glycerin, Dextrin, Amylopectin, Caprylyl Glycol, Ethylhexylglycerin, Xanthan Gum, Pentylene Glycol, Sodium Hydroxide, Isoamyl Laurate, Phenoxyethanol.

Questions or comments

Call toll free

1-800-831-5150 in the US.

PRINCIPAL DISPLAY PANEL - 30 mL Bottle Carton

NEW

Active Clearing

1 US FL OZ / 30 mL e